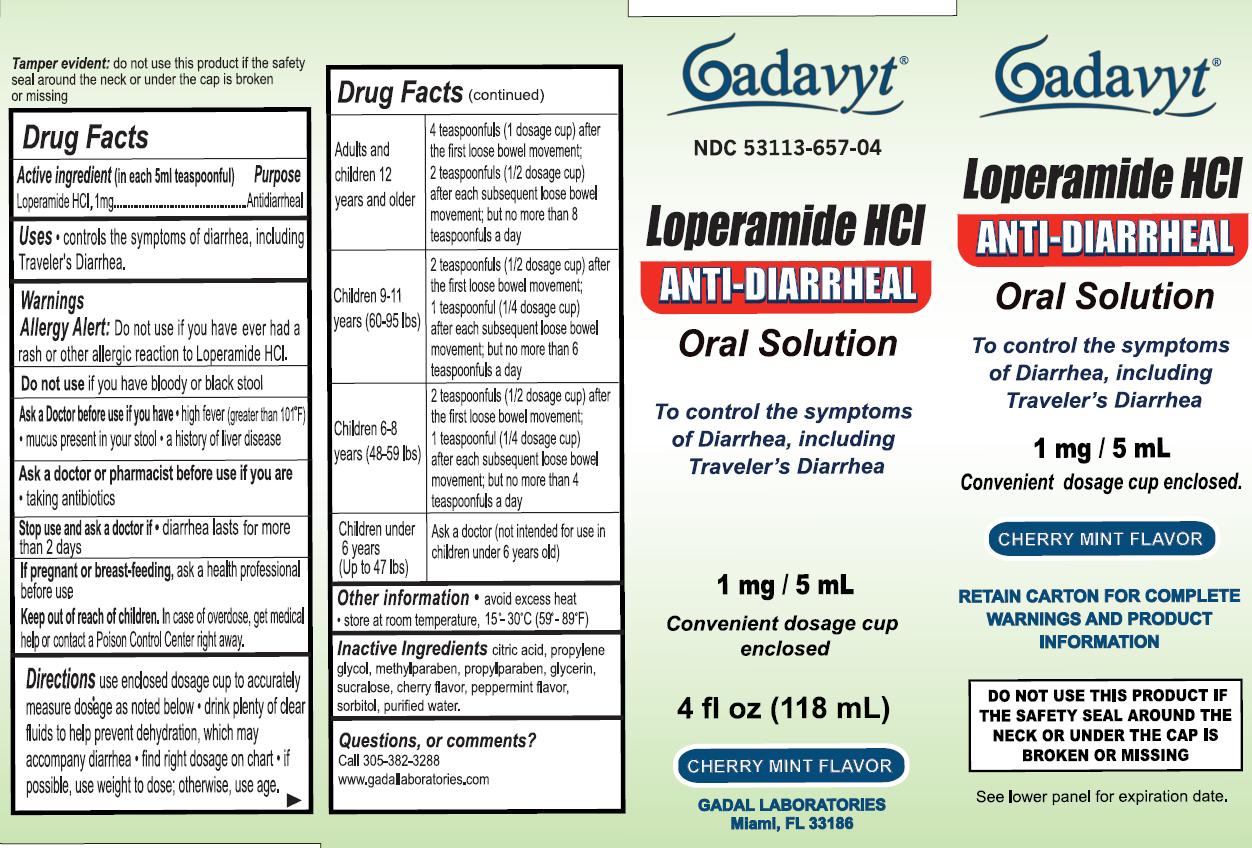 DRUG LABEL: Gadavyt Loperamide HCl
NDC: 53113-657 | Form: LIQUID
Manufacturer: Gadal Laboratories Inc
Category: otc | Type: HUMAN OTC DRUG LABEL
Date: 20130522

ACTIVE INGREDIENTS: LOPERAMIDE HYDROCHLORIDE 1 mg/5 mL
INACTIVE INGREDIENTS: CITRIC ACID MONOHYDRATE; PROPYLENE GLYCOL; METHYLPARABEN; PROPYLPARABEN; GLYCERIN; SUCRALOSE; SORBITOL; WATER

Drug Facts

Active Ingredient (in each 5mL teaspoonful) Purpose

Loperamide HCl, 1mg ....................................................Antidiarrheal

Purpose

Antidiarrheal

Uses

controls the symptoms of diarrhea, including Traveler's Diarrhea.

Warnings

Allergy Alert:Do not use if you have ever had a rash or other allergic reaction to Loperamide HCl.

Do not use if you have bloody or black stool

Ask a Doctor before use if you have

- high fiver (greater than 101 degrees F)
- mucus present in your stool
- a history of liver disease
  Ask a doctor or pharmacist before use if you are taking antibiotics

Stop use and ask a doctor if diarrhea lasts for more than 2 days

Keep out of reach of children. In case of overdose, get medical help or contact Poison Control Center right away.

PREGNANCY OR BREAST FEEDING

If pregnant or breast-feeding,ask a health professional before use

Directions

Use enclosed dosage cup to accurately measure dosage as noted below

- drink plenty of clear fluids to help prevent dehydration, which may accompany diarrhea
- find right dosage on chart
- if possible, use weight to dose; otherwise, use age.

Adults and children 12 years and older | 4 teaspoonfuls (1 dosage cup) after the first loose bowel movement; 2 teaspoonfuls (1/2 dosage cup) after each subsequent loose bowel movement; but no more than 8 teaspoonfuls a day
Children 9-11 (60-95 lbs) | 2 teaspoonfuls (1/2 dosage cup) after the first loose bowel movement; 1 teaspoonful (1/4 dosage cup) after each subsequent loose bowel movement; but no more than 6 teaspoonfuls a day
Children 6-8 (48-59 lbs) | 2 teaspoonfuls (1/2 dosage cup) after the first loose bowel movement; 1 teaspoonfuls (1/4 dosage cup) after each subsequent loose bowel movement; but no more than 4 teaspoonfuls a day
Children under 6 years (Up to 47 lbs) | Ask a doctor (not intended for use in children under 6 years old

Inactive ingredients

citric acid, propylene glycol, methylparaben, propylparaben, glycerin, sucralose, cherry flavor, peppermint flavor, sorbitol, purified water

Questions or comments?

Call 305-382-3288

www.gadallaboratories.com